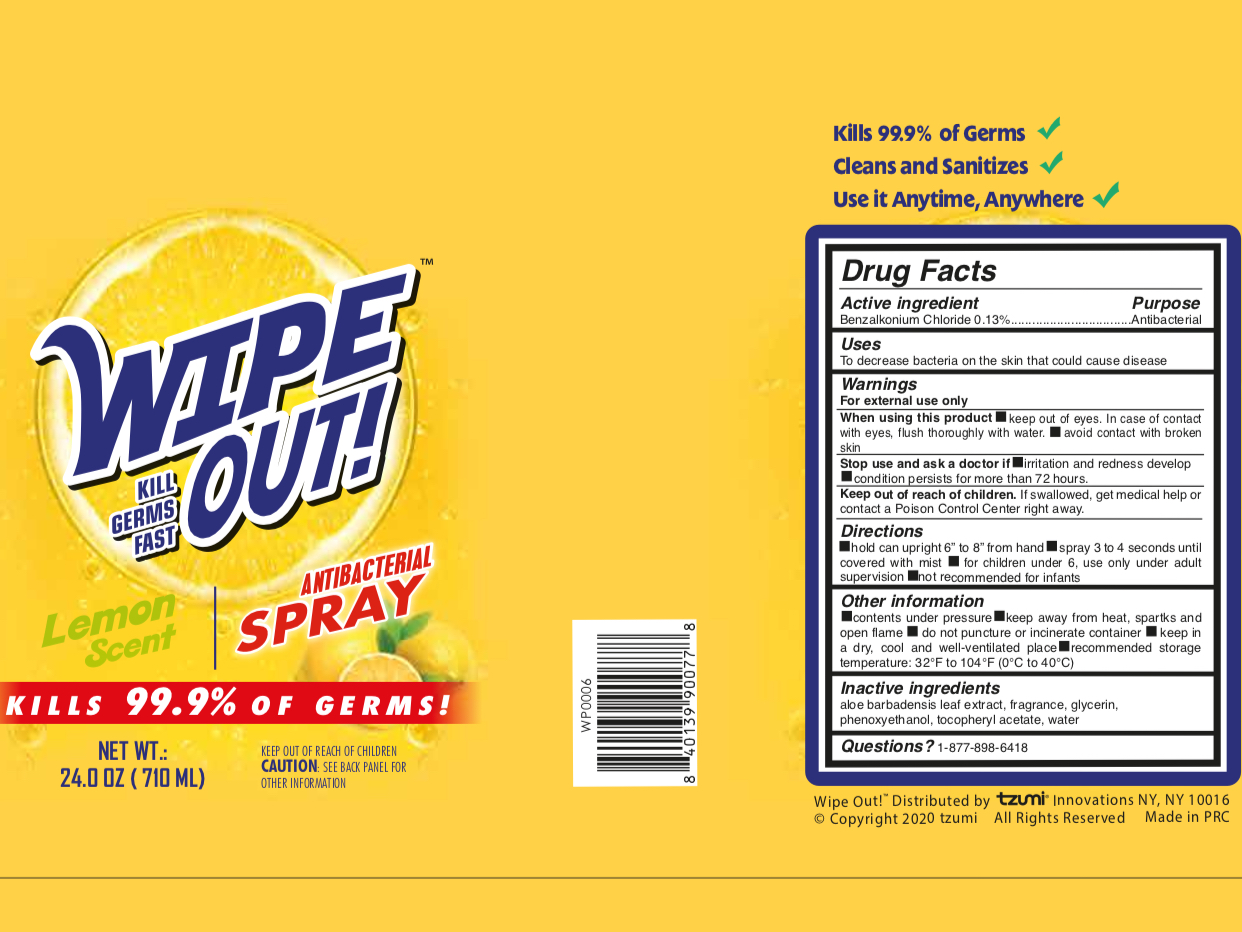 DRUG LABEL: WIPE OUT Lemon Scent ANTIBACTERIAL
NDC: 77878-016 | Form: SPRAY
Manufacturer: TZUMI INNOVATIONS LLC
Category: otc | Type: HUMAN OTC DRUG LABEL
Date: 20201107

ACTIVE INGREDIENTS: BENZALKONIUM CHLORIDE 0.13 g/100 mL
INACTIVE INGREDIENTS: WATER; PHENOXYETHANOL; GLYCERIN; .ALPHA.-TOCOPHEROL ACETATE; ALOE VERA LEAF

77878-016/WP0006, WP0006M

Active Ingredient

Benzalkonium Chloride 0.13%

Purpose

Antibacterial

Use

■ To decrease bacteria on the skin that could cause disease

WARNINGS

For external use only. Flammable.

When using this product,

keep out of eyes. In case of contact with eyes, flush thoroughly with water

Avoid contact with broken skin

Stop use and ask a doctor if irritation or rash occurs. These may be signs of a serious condition

Keep out of reach of children. If swallowed, get medical help or contact a Poison Control Center right away

Directions

Hold can upright 6"-8" from hand.

Spray 3-4 seconds until covered with mist

For children under 6, use only under adult supervision

Not recommended for infants

Other Information

Contents under pressure

Keep away from heat, sparkles, and open flame

Do not puncture or incinerate container

keep in dry, cool and well ventilated place

Recommended storage temperature: 32F-104F (0-40C)

Inactive ingredients

Aloe Barbadensis Leaf Etract, Fragrance, Glycerin, Phenoxyethanol, Tocopheryl Acetate, Water